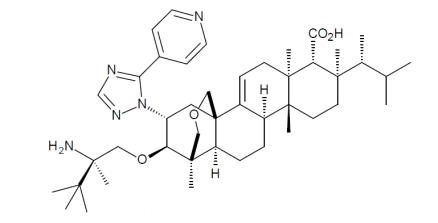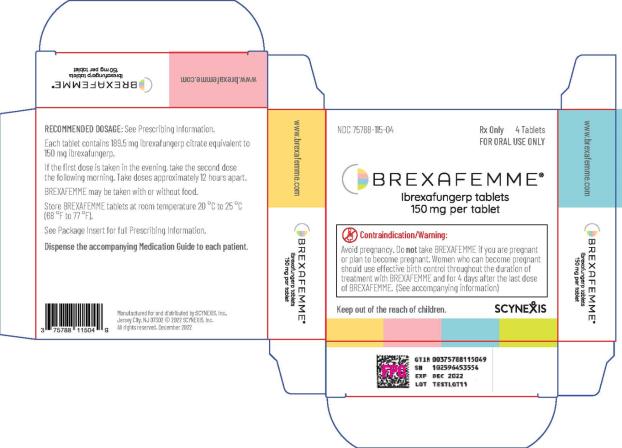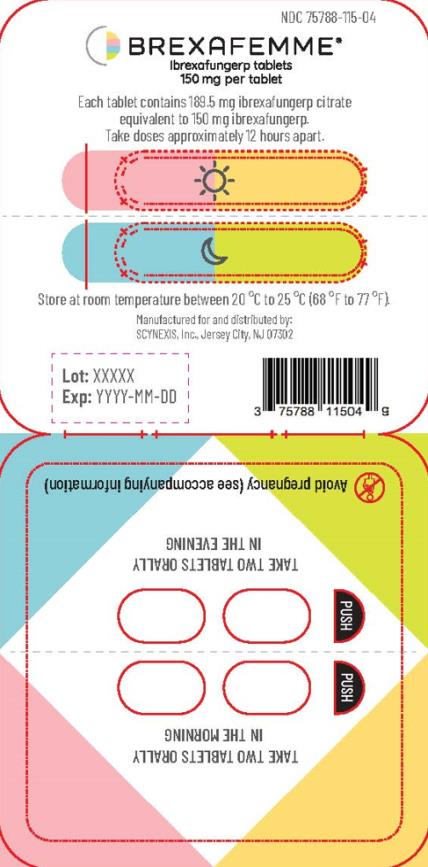 DRUG LABEL: BREXAFEMME
NDC: 75788-115 | Form: TABLET, FILM COATED
Manufacturer: SCYNEXIS, INC.
Category: prescription | Type: HUMAN PRESCRIPTION DRUG LABEL
Date: 20241104

ACTIVE INGREDIENTS: IBREXAFUNGERP CITRATE 150 mg/1 1
INACTIVE INGREDIENTS: BUTYLATED HYDROXYANISOLE; SILICON DIOXIDE; CROSPOVIDONE; MAGNESIUM STEARATE; MANNITOL; MICROCRYSTALLINE CELLULOSE; FD&C BLUE NO. 2; FD&C RED NO. 40; HYDROXYPROPYL CELLULOSE, UNSPECIFIED; TALC; TITANIUM DIOXIDE

HIGHLIGHTS OF PRESCRIBING INFORMATION

These highlights do not include all the information needed to use BREXAFEMME® safely and effectively. See full prescribing information for BREXAFEMME®.
BREXAFEMME® (ibrexafungerp tablets), for oral use
Initial U.S. Approval: 2021

RECENT MAJOR CHANGES

Boxed Warning 11/2022

Indications and Usage (1) 11/2022

Dosage and Administration, (2) 11/2022

WARNING: RISK OF EMBRYO-FETAL TOXICITY

See full prescribing information for the complete boxed warning.

- BREXAFEMME is contraindicated in pregnancy because it may cause fetal harm based on findings from animal reproductive studies. (4, 5.1)
- For females of reproductive potential, verify that the patient is not pregnant prior to initiating treatment. Reassessing pregnancy status prior to each dose is recommended when BREXAFEMME is used monthly for 6 months for reduction in the incidence of recurrent vulvovaginal candidiasis (RVVC). (2.3, 5.1)
- Advise females of reproductive potential to use effective contraception during treatment of vulvovaginal candidiasis (VVC) and throughout the 6-month treatment period for reduction in the incidence of RVVC with BREXAFEMME and for 4 days after the last dose. (5.1, 8.3)

1 INDICATIONS AND USAGE

BREXAFEMME is a triterpenoid antifungal indicated in adult and post-menarchal pediatric females for:

- Treatment of vulvovaginal candidiasis (VVC). (1.1)
- Reduction in the incidence of recurrent vulvovaginal candidiasis (RVVC) (1.1)

2 DOSAGE AND ADMINISTRATION

- Treatment of VVC: The recommended dosage of BREXAFEMME in adult and post-menarchal pediatric females is 300 mg (two tablets of 150 mg) administered approximately 12 hours apart (e.g., in the morning and in the evening) for one day, for a total treatment dosage of 600 mg (four 150 mg tablets). (2.1)
- Reduction in the incidence of RVVC: The recommended dosage of BREXAFEMME in adult and post-menarchal females is 300 mg (two tablets of 150 mg) administered approximately 12 hours apart (e.g., in the morning and in the evening) for one day, for a total daily dosage of 600 mg (four 150 mg tablets) monthly for six months. (2.1)
- BREXAFEMME may be taken with or without food. (2.1)

3 DOSAGE FORMS AND STRENGTHS

Tablets: 150 mg of ibrexafungerp (3)

4 CONTRAINDICATIONS

- Pregnancy (4)
- Hypersensitivity to ibrexafungerp. (4)

6 ADVERSE REACTIONS

- Treatment of VVC: The most frequent adverse reactions (incidence ≥ 2%) reported were diarrhea, nausea, abdominal pain, dizziness, and vomiting. (6.1)
- Reduction in the incidence of RVVC: The most frequent adverse reactions (incidence ≥ 2%) reported were headache, abdominal pain, diarrhea, nausea, urinary tract infection and fatigue. (6.1)

To report SUSPECTED ADVERSE REACTIONS, contact SCYNEXIS, Inc. at 1-888-982-7299 or FDA at 1-800-FDA-1088 or www.fda.gov/medwatch.

7 DRUG INTERACTIONS

- Concomitant use of strong CYP3A inhibitors increases the exposure of ibrexafungerp. Reduce BREXAFEMME dose with concomitant use of a strong CYP3A inhibitor to 150 mg twice daily for one day. (2.2, 7)
- Concomitant use of strong and moderate CYP3A inducers may significantly reduce the exposure of ibrexafungerp. Avoid concomitant administration of BREXAFEMME with strong or moderate CYP3A inducers. (7)

FULL PRESCRIBING INFORMATION

WARNING: RISK OF EMBRYO-FETAL TOXICITY

- BREXAFEMME is contraindicated in pregnancy because it may cause fetal harm based on findings from animal reproductive studies [see Contraindications (4) and Warnings and Precautions (5.1)].
- For females of reproductive potential, verify that the patient is not pregnant prior to initiating BREXAFEMME treatment. Reassessing pregnancy status prior to each dose is recommended when BREXAFEMME is used monthly for 6 months for reduction in the incidence of recurrent vulvovaginal candidiasis (RVVC) [see Dosage and Administration (2.3), Warnings and Precautions (5.1) and Use in Specific Populations (8.3)].
- Advise females of reproductive potential to use effective contraception during treatment of vulvovaginal candidiasis (VVC) and throughout the 6-month treatment period for reduction in the incidence of RVVC with BREXAFEMME and, for 4 days after the last dose [see Warnings and Precautions (5.1) and Use in Specific Populations (8.3)].

1 INDICATIONS AND USAGE

1.1 Vulvovaginal Candidiasis

BREXAFEMME® is indicated in adult and post-menarchal pediatric females for:

● Treatment of vulvovaginal candidiasis (VVC)

● Reduction in the incidence of recurrent vulvovaginal candidiasis (RVVC).

1.2 Usage

If specimens for fungal culture are obtained prior to therapy, antifungal therapy may be instituted before the results of the cultures are known. However, once these results become available, antifungal therapy should be adjusted accordingly.

2 DOSAGE AND ADMINISTRATION

2.1 Recommended Dosage

Treatment of VVC: The recommended dosage of BREXAFEMME in adult and post-menarchal pediatric females is 300 mg (two 150 mg tablets) administered approximately 12 hours apart (e.g., in the morning and in the evening) for one day, for a total daily dosage of 600 mg (four 150 mg tablets).

Reduction in the Incidence of RVVC: The recommended dosage of BREXAFEMME to prevent recurrences is 300 mg (two 150 mg tablets) administered approximately 12 hours apart (e.g., in the morning and in the evening) for one day, for a total daily dosage of 600 mg (four 150 mg tablets) monthly for six months.

BREXAFEMME may be taken with or without food.

2.2 Dosage Modifications in Patients due to Concomitant Use of a Strong Inhibitor of Cytochrome P450 Isoenzymes (CYP) 3A

With concomitant use of a strong CYP3A inhibitor, administer BREXAFEMME 150 mg approximately 12 hours apart (e.g., in the morning and in the evening) for one day. No dosage adjustment is warranted in patients with concomitant use of a weak or moderate CYP3A inhibitor [see Drug Interactions (7) and Clinical Pharmacology (12.3)].

2.3 Pregnancy Evaluation Prior to Initiating Treatment

For females of reproductive potential, verify that the patient is not pregnant prior to initiating treatment with BREXAFEMME. Reassessment of pregnancy status prior to each dose is recommended when BREXAFEMME is used monthly for 6 months for reduction in the incidence of RVVC [see Contraindications (4), Warning and Precautions (5.1) and Use in Specific Populations (8.1, 8.3)].

3 DOSAGE FORMS AND STRENGTHS

BREXAFEMME tablets are purple, oval, biconvex shaped tablets debossed with 150 on one side and SCYX on the other side containing 150 mg of ibrexafungerp.

4 CONTRAINDICATIONS

BREXAFEMME is contraindicated in:

- Pregnancy [see Warnings and Precautions (5.1), and Use in Specific Populations (8.1, 8.3)]
- Patients with hypersensitivity to ibrexafungerp

5 WARNINGS AND PRECAUTIONS

5.1 Risk of Embryo-Fetal Toxicity

Based on findings from animal studies, BREXAFEMME use is contraindicated in pregnancy because it may cause fetal harm. In animal reproduction studies, ibrexafungerp administered orally to pregnant rabbits during organogenesis was associated with fetal malformations including absent forelimb(s), absent hindpaw, absent ear pinna, and thoracogastroschisis at dose exposures greater or equal to approximately 5 times the human exposure at the recommended human dose (RHD).

For females of reproductive potential, verify that the patient is not pregnant prior to initiating treatment with BREXAFEMME. Reassessment of pregnancy status prior to each dose is recommended when BREXAFEMME is used monthly for 6 months for reduction in the incidence of RVVC. Advise females of reproductive potential to use effective contraception during treatment of VVC and throughout the 6-month treatment period for reduction in the incidence of RVVC with BREXAFEMME and, for 4 days after the last dose [see Use in Specific Populations (8.1, 8.3)].

6 ADVERSE REACTIONS

6.1 Clinical Trials Experience

Because clinical trials are conducted under widely varying conditions, adverse reaction rates observed in clinical trials of a drug cannot be directly compared to rates in the clinical trials of another drug and may not reflect the rates observed in practice.

Treatment of VVC

A total of 545 patients were exposed to BREXAFEMME in two clinical trials of post-menarchal females with VVC (Trial 1 and Trial 2). The patients were treated with BREXAFEMME 300 mg (two 150 mg tablets) twice a day, 12 hours apart, for one day. The patients were 18 to 76 years of age (mean 34 years); 69% were White and 28% were Black or African American; 18% were of Hispanic or Latina ethnicity.

The most frequently reported adverse reactions are presented in Table 1.

There were no serious adverse reactions and 2 out of 545 (0.4%) patients discontinued treatment with BREXAFEMME due to vomiting (1 patient) and dizziness (1 patient).

Table 1. Adverse Reactions with Rates ≥2% in BREXAFEMME-Treated Patients with VVC in Trials 1 and 2
Adverse Reaction | BREXAFEMME N = 545 n (%) | Placebo N = 275 n (%)
Diarrhea Nausea Abdominal pain^1 Dizziness^2 Vomiting | 91 (16.7%) 65 (11.9%) 62 (11.4%) 18 (3.3%) 11 (2.0%) | 9 (3.3%) 11 (4.0%) 14 (5.1%) 7 (2.5%) 2 (0.7%)

^1 Includes abdominal pain, abdominal pain upper, abdominal pain lower, and abdominal discomfort

^2 Includes dizziness and postural dizziness

Other Adverse Reactions

The following adverse reactions occurred in < 2% of patients receiving BREXAFEMME in Trial 1 and Trial 2: dysmenorrhea, flatulence, back pain, elevated transaminases, vaginal bleeding, rash/hypersensitivity reaction.

Reduction in the Incidence of RVVC

A total of 130 patients were exposed to BREXAFEMME in a clinical trial of post-menarchal females with RVVC (Trial 3). The patients were treated with BREXAFEMME 300 mg (two 150 mg tablets) twice a day, 12 hours apart, for one day, monthly for six consecutive months. The patients were 18 to 65 years of age (mean 34 years), of which, 59% of patients were between 18 to 35 years, and 41% between 36 to 65 years. Ninety two percent (92%) were White, 7% were Black or African American, and 1% were Asian. Nine percent (9%) of patients were of Hispanic or Latina ethnicity.

The most frequently reported adverse reactions are presented in Table 2.

There were no serious adverse reactions and no patients discontinued treatment with BREXAFEMME due to adverse reaction.

Table 2. Adverse Reactions with Rates ≥2% in BREXAFEMME-Treated Patients with RVVC in Trial 3
Adverse Reaction^1 | BREXAFEMME N = 130 n (%) | Placebo N = 130 n (%)
Headache Abdominal pain^2 Diarrhea Nausea Urinary tract infection Fatigue | 23 (17.6) 13 (10.0) 10 (7.7) 7 (5.4) 5 (3.8) 4 (3.1) | 10 (7.6) 9 (6.9) 5 (3.8) 5 (3.8) 1(0.8) 0

^1 A single patient may have had multiple instances of adverse reactions. Only one episode of adverse reaction is counted per patient

^2 Includes abdominal pain, abdominal pain upper, abdominal pain lower, and abdominal discomfort

7 DRUG INTERACTIONS

Ibrexafungerp is a substrate of CYP3A4. Drugs that inhibit or induce CYP3A may alter the plasma concentrations of ibrexafungerp and affect the safety and efficacy of BREXAFEMME [see Clinical Pharmacology (12.3)]

Table 3 Effect of Coadministered Drugs on Ibrexafungerp Pharmacokinetics:
Concomitant Drugs | Effect on Ibrexafungerp Concentration | Recommendation
Strong CYP3A inhibitors: (e.g., ketoconazole, itraconazole) | Significantly increased | Reduce the BREXAFEMME dosage [see Dosage and Administration (2.2)]
Strong and Moderate CYP3A inducers: (e.g., rifampin, carbamazepine, phenytoin, St. John’s wort, long acting barbiturates, bosentan, efavirenz, or etravirine) | Not studied in vivo or in vitro, but likely to result in significant reduction | Avoid concomitant administration

Ibrexafungerp is an inhibitor of CYP3A4, P-gp and OATP1B3 transporter [(see Clinical Pharmacology (12.3)]. However, given the short treatment duration for VVC, the effect of BREXAFEMME on the pharmacokinetics of substrates of CYP3A4, P-gp and OATP1B3 transporters is not considered to be clinically significant.

8 USE IN SPECIFIC POPULATIONS

8.1 Pregnancy

Risk Summary

Based on findings from animal studies, BREXAFEMME use is contraindicated in pregnancy because it may cause fetal harm. In pregnant rabbits, oral ibrexafungerp administered during organogenesis was associated with rare malformations including absent forelimb(s), absent hindpaw, absent ear pinna, and thoracogastroschisis at dose exposures greater or equal to approximately 5 times the human exposure at the RHD. Oral ibrexafungerp administered to pregnant rats during organogenesis was not associated with fetal toxicity or increased fetal malformations at a dose exposure approximately 5 times the human exposure at the RHD (see Data). Available data on BREXAFEMME use in pregnant women are insufficient to draw conclusions about any drug-associated risks of major birth defects, miscarriage, or other adverse maternal or fetal outcomes.

There is a pregnancy safety study for BREXAFEMME. If BREXAFEMME is inadvertently administered during pregnancy or if pregnancy is detected within 4 days after a patient receives BREXAFEMME, pregnant women exposed to BREXAFEMME and healthcare providers should report pregnancies to SCYNEXIS, Inc. at 1-888-982-SCYX (7299).

Data

Animal Data

In a rat embryo-fetal study, ibrexafungerp was administered to pregnant rats by oral gavage from gestation days (GDs) 6 through 17 at doses of 10, 20, 35, and 50 mg/kg/day. No fetal malformations or changes in embryo-fetal survival or fetal body weights occurred with any of the doses of ibrexafungerp up to the high-dose of 50 mg/kg/day (approximately 5 times the RHD based on plasma AUC comparison).

In an embryo-fetal study in rabbits, ibrexafungerp was administered by oral gavage at doses of 10, 25, and 50 mg/kg/day from GD 7 through GD 19. In the mid-dose group administered 25 mg/kg/day (approximately 5 times the RHD based on AUC comparison), fetal malformations, including absent ear pinna, craniorachischisis, thoracogastroschisis, trunk kyphosis, absent forelimbs, absent forepaws, and absent hindpaw occurred in a single fetus. Malformations including absent hindpaw and anencephaly occurred with an increased litter incidence in the high-dose group of 50 mg/kg/day (approximately 13 times the RHD based on AUC comparison), and other malformations occurred in single fetuses and litters including absent ear pinna, thoracogastroschisis, absent forelimb, and absent thyroid gland. No changes in embryo-fetal survival or fetal body weights were observed with any of the ibrexafungerp doses, and fetal malformations were not observed with the 10 mg/kg/day dose of ibrexafungerp (approximately 2 times the RHD based on AUC comparison).

In a pre-postnatal study in rats, ibrexafungerp was administered by oral gavage from GD 6 through the lactation period until lactation day 20 in maternal doses of 10, 20, 35, and 50 mg/kg/day. No maternal toxicity or adverse effects on the survival, growth, behavior, or reproduction of first-generation offspring occurred with any of the ibrexafungerp doses up to the high dose of 50 mg/kg/day (approximately 5 times the RHD based on AUC comparison).

8.2 Lactation

Risk Summary

There are no data on the presence of ibrexafungerp in either human or animal milk, the effects on the breast-fed infant, or the effects on milk production.

The developmental and health benefits of breastfeeding should be considered along with the mother’s clinical need for BREXAFEMME and any potential adverse effects on the breastfed child from BREXAFEMME or from the underlying maternal condition.

8.3 Females and Males of Reproductive Potential

Based on animal data, BREXAFEMME may cause fetal harm when administered to a pregnant female [see Use in Specific Populations (8.1)].

Pregnancy Testing

For females of reproductive potential, verify that the patient is not pregnant prior to initiating treatment with BREXAFEMME. Reassessment of pregnancy status prior to each dose is recommended when BREXAFEMME is used monthly for 6 months for reduction in the incidence of RVVC [see Dosage and Administration (2.3), Contraindications (4) and Use in Specific Populations (8.1)].

Contraception

Females

For treatment of VVC, advise females of reproductive potential to use effective contraception during treatment with BREXAFEMME and for 4 days after the last dose.

For reduction in the incidence of RVVC, advise females of reproductive potential to use effective contraception throughout the 6-month treatment period with BREXAFEMME and, for 4 days after the last dose.

8.4 Pediatric Use

The safety and effectiveness of BREXAFEMME for treatment of VVC have been established in post-menarchal pediatric females. BREXAFEMME is also indicated for the reduction in the incidence of RVVC [ see Indications and Usage (1.1)]. Use of BREXAFEMME in post-menarchal pediatric patients is supported by evidence from adequate and well-controlled studies of BREXAFEMME in adult non-pregnant women with additional pharmacokinetic and safety data from post-menarchal pediatric females [see Adverse Reactions (6.1), Clinical Pharmacology (12.3) and Clinical Studies (14.1)].

The safety and effectiveness of BREXAFEMME have not been established in pre-menarchal pediatric females.

8.5 Geriatric Use

Clinical studies with ibrexafungerp did not include sufficient numbers of subjects aged 65 and older to determine whether they respond differently from younger subjects. No clinically meaningful differences in the pharmacokinetics of ibrexafungerp were observed in geriatric patients compared to younger adults [see Clinical Pharmacology (12.3)].

8.6 Hepatic Impairment

No dosage adjustment of BREXAFEMME is recommended in patients with mild hepatic impairment (Child-Pugh Class A) or moderate hepatic impairment (Child-Pugh Class B).

Administration of BREXAFEMME in patients with severe hepatic impairment (Child-Pugh Class C) has not been studied. [see Clinical Pharmacology (12.3)].

10 OVERDOSAGE

There is no experience with overdosage of BREXAFEMME.

There is no specific antidote for ibrexafungerp. Treatment should be supportive with appropriate monitoring.

11 DESCRIPTION

BREXAFEMME, available as an oral tablet, contains ibrexafungerp citrate, a triterpenoid antifungal agent.

Ibrexafungerp is designated chemically as (1S,4aR,6aS,7R,8R,10aR,10bR,12aR,14R,15R)-15-[(2R)-2-amino-2,3,3-trimethylbutoxy]-1,6a,8,10a-tetramethyl-8-[(2R)-3-methylbutan-2-yl]-14-[5-(pyridine-4-yl)-1H-1,2,4-triazol-1-yl]-1,6,6a,7,8,9,10,10a,10b,11,12,12a-dodecahydro-2H,4H-1,4a-propanophenanthro[1,2-c]pyran-7-carboxylic acid compound with 2-hydroxypropane-1,2,3-tricarboxylic acid (1:1) with an empirical formula of C44H67N5O4 • C6H8O7 and a molecular weight of 922.18 grams per mole. The chemical structure is:

• C6H8O7

BREXAFEMME tablet for oral administration is a purple, oval, biconvex shaped, film-coated tablet containing 189.5 mg of ibrexafungerp citrate equivalent to 150 mg of ibrexafungerp. In addition to the active ingredient, the tablet formulation contains butylated hydroxyanisole, colloidal silicon dioxide, crospovidone, magnesium stearate, mannitol, and microcrystalline cellulose. The tablet film-coating contains FD&C Blue #2, FD&C Red #40, hydroxypropyl cellulose, hydroxypropylmethyl cellulose 2910, talc and titanium dioxide.

12 CLINICAL PHARMACOLOGY

12.1 Mechanism of Action

Ibrexafungerp is a triterpenoid antifungal drug [see Microbiology (12.4)].

12.2 Pharmacodynamics

Ibrexafungerp exposure-response relationships and the time course of pharmacodynamic response are unknown.

Cardiac Electrophysiology

At a concentration of 5 times or greater than that achieved after a single day 300 mg twice daily dose, ibrexafungerp does not prolong the QTc interval to any clinically relevant extent.

12.3 Pharmacokinetics

In healthy subjects, ibrexafungerp area under the curve (AUC) and maximal concentration (Cmax) increased approximately dose-proportionally following single dose administration from 10 to 1600 mg (0.02 to 2.67 times the approved recommended daily dose) and multiple-dose administration from 300-800 mg (0.50 to 1.33 times the approved recommended daily dose).

Based on a population pharmacokinetic analysis in patients with VVC, the model predicts that 300 mg twice a day for 2 doses achieves a mean (%CV) AUC0-24 exposure of 6832 (15%) ng•hr/mL and Cmax of 435 (15%) ng/mL under fasted conditions and a mean AUC0-24 exposure of 9867 (15%) ng•h/mL and Cmax of 629 (15%) ng/mL under fed conditions.

Absorption

After oral administration of BREXAFEMME in healthy volunteers, ibrexafungerp generally reaches maximum plasma concentrations 4 to 6 hours after single and multiple dosing.

Effect of Food

Following administration of BREXAFEMME to healthy volunteers, the ibrexafungerp Cmax increased 32% and the AUC increased 38% with a high fat meal (800-1000 calories; 50% fat), compared to fasted conditions. This exposure change is not considered clinically significant [see Dosage and Administration (2.1)].

Distribution

The mean steady state volume of distribution (Vss) of ibrexafungerp is approximately 600 L. Ibrexafungerp is highly protein bound (greater than 99%), predominantly to albumin. Animal studies demonstrate a 9-fold higher exposure in vaginal tissue than in blood.

Elimination

Ibrexafungerp is eliminated mainly via metabolism and biliary excretion. The elimination half-life is approximately 20 hours.

Metabolism

In vitro studies show that ibrexafungerp undergoes hydroxylation by CYP3A4, followed by glucuronidation and sulfation of a hydroxylated inactive metabolite.

Excretion

Following oral administration of radio-labeled ibrexafungerp to healthy volunteers, a mean of 90% of the radioactive dose (51% as unchanged ibrexafungerp) was recovered in feces and 1% was recovered in urine.

Specific Populations

Post-Menarchal Pediatric Females and Geriatric Patients

The pharmacokinetics of ibrexafungerp were not altered in post-menarchal pediatric females (ages 13 to 17 years) or in geriatric patients (ages 65 to 76 years).

Patients with Hepatic Impairment

The pharmacokinetics of ibrexafungerp were not altered in subjects with mild (Child-Pugh Class A) to moderate (Child-Pugh Class B) hepatic impairment when the total AUC estimates were compared to healthy subjects.

The impact of severe hepatic impairment (Child-Pugh Class C) on the pharmacokinetics of ibrexafungerp is unknown.

Drug Interaction Studies

Ibrexafungerp is a substrate of CYP3A4 and P-gp. In vitro, ibrexafungerp is an inhibitor of CYP2C8, CYP3A4, P-gp transporter, and OATP1B3 transporter. Ibrexafungerp is not an inducer of CYP3A4.

The effect of coadministration of drugs on the pharmacokinetics of ibrexafungerp and the effect of ibrexafungerp on the pharmacokinetics of coadministered drugs were studied in healthy subjects.

Effect of Coadministered Drugs on Ibrexafungerp Pharmacokinetics

Strong CYP 3A4 Inhibitor: Ketoconazole (400 mg once daily for 15 days), a strong CYP3A4 and P-gp inhibitor, increased the ibrexafungerp AUC by 5.8-fold and Cmax by 2.5-fold [see Drug Interactions (7)].

Moderate CYP3A4 Inhibitor: Diltiazem (240 mg once daily for 15 days) increased the ibrexafungerp AUC by 2.5-fold and Cmax by 2.2-fold. This exposure change is not considered clinically significant at the approved recommended dosage for VVC.

Proton Pump Inhibitor: Pantoprazole (40 mg once daily for 5 days) decreased ibrexafungerp AUC by approximately 25% and Cmax by 22%. This exposure change is not considered clinically significant at the approved recommended dosage for VVC.

Effect of Ibrexafungerp on the Pharmacokinetics of Coadministered Drugs

The effects of ibrexafungerp on substrates of CYP2C8, CYP3A4, P-gp, and OATP1B3 transporters were evaluated in studies that included loading doses of ibrexafungerp of 1250 to 1500 mg (2.1 to 2.5 times the approved recommended daily dose) for two days followed by 750 mg (1.25 times the approved recommended daily dose) once daily for 3-7 days.

CYP2C8 substrates: Ibrexafungerp did not increase the AUC0-inf or Cmax of rosiglitazone, a moderate sensitive CYP2C8 substrate.

CYP3A4 substrates: Ibrexafungerp resulted in 1.4-fold increase in the AUC0-inf and no effect on the Cmax of the sensitive CYP3A4 and P-gp substrate tacrolimus.

P-gp substrates: Ibrexafungerp resulted in a 1.4-fold increase in the AUC0-48 and a 1.25-fold increase in the Cmax of the P-gp substrate dabigatran.

OATP1B3 transporters: Ibrexafungerp resulted in a 2.8-fold increase in the AUC0-24 and a 3.5 fold increase in the Cmax of the OATP1B3 transporter substrate pravastatin.

12.4 Microbiology

Mechanism of Action

Ibrexafungerp, a triterpenoid antifungal agent, inhibits glucan synthase, an enzyme involved in the formation of 1,3-β-D-glucan, an essential component of the fungal cell wall.

Ibrexafungerp has concentration-dependent fungicidal activity against Candida species as measured by time kill studies. Ibrexafungerp retains in vitro antifungal activity when tested at pH 4.5 (the normal vaginal pH).

Resistance

The potential for resistance to ibrexafungerp has been evaluated in vitro and is associated with mutations of the fks-2 gene; the clinical relevance of these findings is unknown. Ibrexafungerp retains activity against most fluconazole resistant Candida spp. No resistance development was observed after monthly BREXAFEMME dosing in patients with RVVC.

Interaction with Other Antifungals

In vitro studies have not demonstrated antagonism between ibrexafungerp and azoles or echinocandins.

Antimicrobial Activity

Ibrexafungerp has been shown to be active against most isolates of the following microorganism both in vitro and in clinical infections [see Indications and Usage (1)]:

Candida albicans

The following in vitro data are available, but their clinical significance is unknown. Ibrexafungerp has in vitro activity against most isolates of the following microorganisms:

Candida auris

Candida dubliniensis

Candida glabrata

Candida guilliermondii

Candida keyfr

Candida krusei

Candida lusitaniae

Candida parapsilosis

Candida tropicalis

13 NONCLINICAL TOXICOLOGY

13.1 Carcinogenesis, Mutagenesis, Impairment of Fertility

Carcinogenesis

Two-year carcinogenicity studies of ibrexafungerp have not been performed.

Mutagenesis

No mutagenic or clastogenic effects were detected in an in vitro bacterial reverse mutation assay, an in vitro chromosomal aberration assay, and an in vivo bone marrow micronucleus assay in rats.

Impairment of Fertility

In a male and female fertility study in rats, ibrexafungerp was administered to male rats by oral gavage in doses of 10, 20, 40, and 80 mg/kg/day for 28 days before mating and throughout mating and to female rats for 15 days before mating, during mating, and until gestation day (GD) 6. Ibrexafungerp did not impair fertility in either sex at any dose up to the highest dose of 80 mg/kg/day (approximately 10 times the RHD based on AUC comparison).

13.2 Animal Toxicity and/or Pharmacology

Daily administration of oral ibrexafungerp for 26 weeks in rats, at the highest dose of 80 mg/kg/day (approximately 10 times the RHD based on AUC comparison), was associated with marked, but reversible, phospholipidosis and foamy histiocytes in alveolar tissue in the lung and labored breathing, marked irritation and metaplasia in gastric mucosa, and peripheral nerve degeneration accompanied by hind-limb paralysis.

14 CLINICAL STUDIES

14.1 Treatment of VVC

Two randomized placebo-controlled clinical trials (Trial 1, NCT03734991 and Trial 2, NCT03987620) with a similar design were conducted to evaluate the safety and efficacy of a single day of BREXAFEMME 600 mg (two 150 mg tablets per dose, administered 12 hours apart) for the treatment of VVC. Non-pregnant post-menarchal females with a diagnosis of VVC were eligible. A diagnosis of VVC was defined as (a) minimum composite vulvovaginal signs and symptoms (VSS) score of ≥4 with at least two signs or symptoms having a score of 2 (moderate) or greater; (b) positive microscopic examination with 10% KOH in a vaginal sample revealing yeast forms (hyphae/pseudohyphae) or budding yeasts, and (c) normal vaginal pH (≤4.5). The total composite VSS score was based on the vulvovaginal signs (erythema, edema, excoriation) and vulvovaginal symptoms (itching, burning, or irritation) where each was scored as 0= absent, 1= mild, 2= moderate, or 3= severe. Study visits included the test of cure (TOC, Day 8 to 14) visit and a follow-up (Day 21 to 29) visit. The modified intent to treat (MITT) population included randomized subjects with a baseline culture positive for Candida species who took at least 1 dose of study medication.

Trial 1 was conducted in the United States. The MITT population consisted of 190 patients treated with BREXAFEMME and 100 patients treated with placebo. The average age was 34 years (range 17-67 years), with 91% less than 50 years. Fifty-four percent (54%) were White and 40% were Black or African American, 26% were of Hispanic or Latino ethnicity. The average BMI was 30 and 9% had a history of diabetes. The median VSS score at baseline was 9 (range 4-18). The majority (92%) of the subjects were culture-positive with C. albicans.

Trial 2 was conducted in the United States (39%) and Bulgaria (61%). The MITT population consisted of 189 patients treated with BREXAFEMME and 89 patients treated with placebo. The average age was 34 years (range 18-65 years), with 92% less than 50 years. Eighty-one percent (81%) were White and 19% were Black or African American, 10% were of Hispanic or Latino ethnicity. The average BMI was 26 and 5% had a history of diabetes. The median VSS score at baseline was 10 (range 4-18). The majority (89%) of the subjects were culture-positive with C. albicans.

Efficacy was assessed by clinical outcome at the TOC visit. A complete clinical response was defined as the complete resolution of signs and symptoms (VSS score of 0). Additional endpoints included a negative culture for Candida spp. at the TOC visit, and clinical outcome at the follow-up visit.

Statistically significantly greater percentages of patients experienced a complete clinical response at TOC, negative culture at TOC, and complete clinical response at follow-up with treatment with BREXAFEMME compared to placebo. The results for the clinical and mycological responses are presented in Table 4.

Table 4. Clinical and Mycological Response in Post-menarchal Females with VVC in Trials 1 and 2, MITT Population
 | Trial 1 |  | Trial 2
 | BREXAFEMME N = 190 n (%) | Placebo N = 100 n (%) | BREXAFEMME N = 189 n (%) | Placebo N = 89 n (%)
Complete Clinical Response at TOC^1 | 95 (50.0) | 28 (28.0) | 120 (63.5) | 40 (44.9)
Difference (95% CI) P-value | 22.0 (10.2, 32.8) 0.001 |  | 18.6 (6.0, 30.6) 0.009
Negative Culture at TOC | 94 (49.5) | 19 (19.0) | 111 (58.7) | 26 (29.2)
Difference (95% CI) P-value | 30.5 (19.4, 40.3) < 0.001 |  | 29.5 (17.2, 40.6) < 0.001
Complete Clinical Response at follow-up^2 | 113 (59.5) | 44 (44.0) | 137 (72.5) | 44 (49.4)
Difference (95% CI) P-value | 15.5 (3.4, 27.1) 0.007 |  | 23.1 (10.8, 35.0) 0.006

^1Absence of signs and symptoms (VSS Score of 0) without need for additional antifungal therapy or topical drug therapy for the treatment of vulvovaginal symptoms at test of cure (TOC) visit.

^2Absence of signs and symptoms (VSS Score of 0) without need for further antifungal treatment or topical drug therapy for the treatment of vulvovaginal symptoms prior to follow-up visit.

14.2 Reduction in the Incidence of RVVC

A randomized placebo-controlled clinical trial (Trial 3, NCT04029116) was conducted to evaluate the safety and efficacy of BREXAFEMME 300 mg (two 150 mg tablets) administered approximately 12 hours apart (e.g., in the morning and in the evening) for one day, for a total daily dosage of 600 mg (four 150 mg tablets) administered once monthly for six months. Trial 3 was conducted in the United States (33%), Bulgaria (28%), Poland (12%), and Russia (28%). Non-pregnant post-menarchal females presenting with a symptomatic VVC episode and a history of recurrent VVC (at least 3 episodes of VVC in the previous 12 months) were eligible. The symptomatic episode at Screening was treated with 3 doses of fluconazole 150 mg 3 days apart.

To be randomized, patients had to have a culture-confirmed VVC episode at Screening and had to achieve significant resolution of their vulvovaginal signs and symptoms (defined as a total composite score ≤ 2 on the VSS Scale) after fluconazole treatment. Patients were randomized at a 1:1 ratio to receive double-blind BREXAFEMME or placebo administered as a single-day treatment repeated every 4 weeks for a total of 6 single-day treatments. Study visits included the test of cure (TOC) at Week 24 (4 weeks after the last dose) and a follow-up visit at Week 36. The intent to treat (ITT) population was all randomized patients.

The ITT population consisted of 130 patients treated with BREXAFEMME and 130 patients treated with placebo. The average age was 34 years (range 18-65 years) with 95% less than 50 years. Ninety percent (90%) of patients were White, 8% were Black or African American, and 2% were Asian and other race. Eight percent (8%) of patients were of Hispanic or Latino ethnicity. The average BMI of the patient population was 25 and 16.5% were obese (BMI >30).

Efficacy was assessed as the percentage of patients with Clinical Success, defined as subjects with No Culture Proven, Presumed or Suspected Recurrence of VVC requiring antifungal therapy up to TOC at Week 24. Clinical success was also assessed at the Week 36 Follow-up visit.

Statistically significantly greater percentages of patients experienced Clinical Success at TOC compared to placebo. The clinical success rate at TOC was lower for patients in the United States when compared to patients outside the United States (ex-US) for both BREXAFEMME and placebo groups. In both regions, the BREXAFEMME group had a higher clinical success rate compared to placebo (US: 33% vs 23% and ex-US: 81% vs 68% in BREXAFEMME vs placebo arms, respectively) and the difference between the treatment groups was consistent [US: 10.1% (-9.0, 29.1) and ex-US: 12.9% (0.04, 25.7)]. Clinical Success at Week 36 was also greater for BREXAFEMME compared to placebo. The results for clinical success and reasons for clinical failure are presented in Table 5.

Table 5. Clinical and Mycological Response in Post-menarchal Females with RVVC in Trial 3, ITT Population
 | Trial 3
 | BREXAFEMME N = 130 n (%) | Placebo N = 130 n (%) | Difference (95% CI) P-value
Clinical success at TOC (Week 24) | 85 (65.4) | 69 (53.1) | 12.7 (2.2, 23.1) 0.020
Reasons For Clinical Failure at TOC Mycologically Proven Recurrence Presumed Recurrence Suspected Recurrence Imputed Recurrence^1 | 30 (23.1) 7 (5.4) 2 (1.5) 6 (4.6) | 47 (36.2) 3 (2.3) 4 (3.1) 7 (5.4)
Clinical success at Week 36 Follow Up Visit | 75 (57.7) | 60 (46.2) | 11.9 (1.1, 22.6) 0.034
Reasons For Clinical Failure at Week-36 Follow-up Visit Mycologically Proven Recurrence Presumed Recurrence Suspected Recurrence Imputed Recurrence^1 | 37 (28.5) 8 (6.2) 4 (3.1) 6 (4.6) | 51 (39.2) 5 (3.8) 5 (3.8) 9 (6.9)

Abbreviations: CI = confidence interval; TOC = test of cure.

^1Imputed recurrences are subjects whose clinical outcome cannot be determined due to early termination or missing critical efficacy assessment at TOC.

16 HOW SUPPLIED / STORAGE AND HANDLING

16.1 How Supplied

BREXAFEMME (ibrexafungerp tablets) are purple, oval, biconvex shaped tablets debossed with 150 on one side and SCYX on the other side. Each tablet contains 150 mg ibrexafungerp (equivalent to 189.5 mg of ibrexafungerp citrate).

Tablets are packaged in polyvinyl/polyvinylidene chloride child-resistant blister packs, four (4) tablets per pack. (NDC 75788-115-04)

16.2 Storage and Handling

Store BREXAFEMME tablets at 20°C to 25°C (68°F to 77°F). Brief exposure to 15°C to 30°C (59°F to 86°F) permitted (see USP Controlled Room Temperature).

17 PATIENT COUNSELING INFORMATION

Advise the patient to read the FDA approved patient labeling (Medication Guide)

Risk of Embryo-Fetal Toxicity

- Advise patients that BREXAFEMME is contraindicated in pregnancy since it may cause fetal harm. [see Warnings and Precautions (5.1) and Use in Specific Populations (8.1)].
- Inform females of reproductive potential that their healthcare provider will verify that they are no pregnant prior to initiating BREXAFEMME treatment.
- Advise females of reproductive potential that reassessing pregnancy status prior to each is recommended when BREXAFEMME is used monthly for 6 months for reduction in the incidence of RVVC.
- For treatment of VVC, advise females of reproductive potential to use effective contraception while taking BREXAFEMME and for 4 days after the last dose [see Use in Specific Populations (8.3)].
- For reduction in the incidence of RVVC, advise females of reproductive potential to use effective contraception throughout the 6-month treatment period with BREXAFEMME and for 4 days after the last dose [see Use in Specific Populations (8.3)].
- Advise females to inform their healthcare provider of a known or suspected pregnancy [see Warnings and Precautions (5.1) and Use in Specific Populations (8.1)].
- Advise patients who have inadvertently taken BREXAFEMME during pregnancy that there is a pregnancy safety study that monitors pregnancy outcomes. Encourage these patients to report their pregnancy to SCYNEXIS, Inc. at 1-888-982-7299 [see Use in Specific Populations (8.1)].

Important Administration Instructions

For treatment of VVC, inform the patient that each BREXAFEMME dose consists of two tablets. A total treatment course for VVC is two doses taken approximately 12 hours apart and consists of a total of four tablets.

For reduction in the incidence of RVVC, inform the patients that the total treatment course is for six months. Each dose consists of two tablets taken approximately 12 hours apart for a total daily dosage of four tablets, taken monthly for six months.

If the first two tablets are taken in the morning, the second two tablets should be taken that same day in the evening. If the first two tablets are taken in the afternoon or evening, the second two tablets should be taken the following morning.

Inform the patient that BREXAFEMME can be taken with or without food [see Dosage and Administration (2.1)].

Concomitant Medications

Advise the patient to inform their health care provider if they are taking any other medications as certain medications can increase or decrease blood concentrations of BREXAFEMME or BREXAFEMME may increase or decrease blood concentrations of certain medications [see Dosage and Administration (2.2)].

Manufactured for:
SCYNEXIS, Inc.
Jersey City, NJ

Patent: www.scynexis.com/product/patent

BREXAFEMME® is a registered trademark of SCYNEXIS, Inc.

MEDICATION GUIDE
BREXAFEMME® [brex a fem]
(ibrexafungerp tablets) for oral use

What is the most important information I should know about BREXAFEMME?
BREXAFEMME may cause serious side effects, including:

- Harm to your unborn baby. Treatment with BREXAFEMME during pregnancy can cause harm to your unborn baby.

Women who can become pregnant may be asked by their healthcare provider to take a pregnancy test before each treatment with BREXAFEMME. Women who can become pregnant should use effective birth control throughout the duration of treatment with BREXAFEMME and for 4 days after the last dose of BREXAFEMME. Talk to your healthcare provider about birth control methods that may be right for you.
See “Do not take BREXAFEMME if you:”

What is BREXAFEMME?

- BREXAFEMME is a prescription medicine used to treat vaginal yeast infection and reduce the number of recurrent vaginal yeast infections in adults and adolescent females who have started their menstruation.
- It is not known if BREXAFEMME is safe and effective in pre-adolescent females who have not started their menstruation.

Do not take BREXAFEMME if you:

- Are pregnant or plan to become pregnant. BREXAFEMME may harm your unborn baby. Tell your healthcare provider if you are pregnant, think you might be pregnant, or plan to become pregnant.
- Are allergic to ibrexafungerp.

Before you take BREXAFEMME, tell your healthcare provider about all of your medical conditions, including if you:

- Are breastfeeding or plan to breastfeed. It is not known if BREXAFEMME passes into your breast milk. You and your healthcare provider should decide if you will take BREXAFEMME or breast feed.

BREXAFEMME may affect the way other medicines work, and other medicines may affect how BREXAFEMME works.
Tell your healthcare provider about all the medicines you take, including prescription and over-the-counter medicines, vitamins, and herbal supplements.

How should I take BREXAFEMME?

- Take BREXAFEMME exactly as your healthcare provider tells you to take it.
- Take BREXAFEMME tablets by mouth with or without food.

What are the possible side effects of BREXAFEMME?

- See “What is the most important information I should know about BREXAFEMME?”

The most common side effects of BREXAFEMME include headache, loose stools, nausea, stomach pain, dizziness, and vomiting.
These are not all the possible side effects of BREXAFEMME.
Call your doctor for medical advice about side effects. You may report side effects to FDA at 1-800-FDA-1088.

How should I store BREXAFEMME?

- Store BREXAFEMME at room temperature between 68°F to 77°F (20°C to 25°C).
- BREXAFEMME is supplied in child resistant packaging.

Keep BREXAFEMME and all medicines out of reach of children.

General information about the safe and effective use of BREXAFEMME.
Medicines are sometimes prescribed for purposes other than those listed in a Medication Guide. Do not use BREXAFEMME for a condition for which it was not prescribed. Do not give BREXAFEMME to other people even if they have the same symptoms that you have. It may harm them. You can ask your pharmacist or healthcare provider for information about BREXAFEMME that is written for health professionals.

What are the ingredients in BREXAFEMME?
Active ingredient: ibrexafungerp
Inactive ingredients:
Tablet core: butylated hydroxyanisole, colloidal silicon dioxide, crospovidone, magnesium stearate, mannitol, and microcrystalline cellulose. Tablet film coating: FD&C Blue #2, FD&C Red #40, hydroxypropyl cellulose, hydroxypropylmethyl cellulose 2910, talc and titanium dioxide.
BREXAFEMME is a registered trademark of SCYNEXIS, Inc.
Manufactured for: SCYNEXIS, Inc., Jersey City, New Jersey, 07302
©2022 SCYNEXIS, Inc.
For more information, call 1-888-982-SCYX (7299) or go to www.brexafemme.com

This Medication Guide -has been approved by the U.S. Food and Drug Administration Revised: 11/2022

PRINCIPAL DISPLAY PANEL

NDC 75788-115-04
Rx Only
4 Tablets
FOR ORAL USE ONLY
BREXAFEMME
150 mg per tablet

PRINCIPAL DISPLAY PANEL

NDC 75788-115-04
Rx Only
Blister Pack
BREXAFEMME
150 mg per tablet